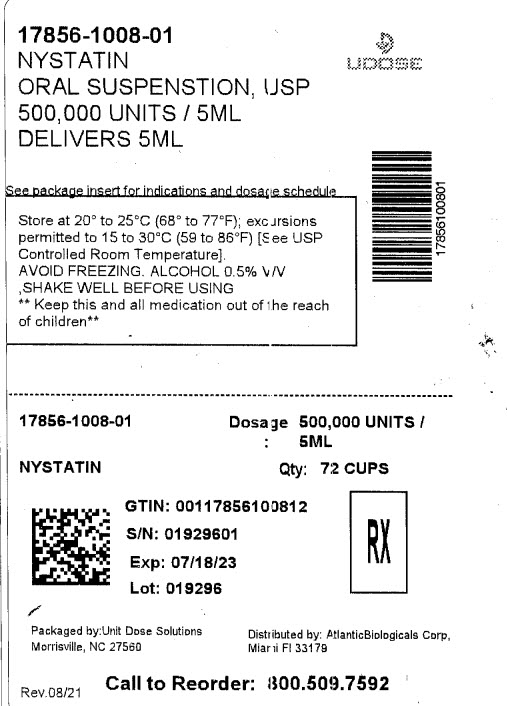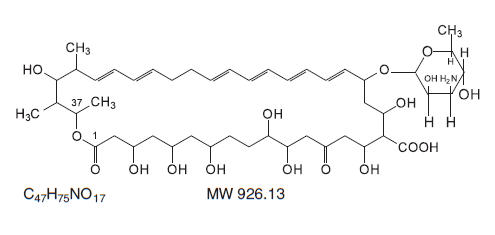 DRUG LABEL: Nystatin
NDC: 17856-1008 | Form: SUSPENSION
Manufacturer: ATLANTIC BIOLOGICALS CORP.
Category: prescription | Type: HUMAN PRESCRIPTION DRUG LABEL
Date: 20230119

ACTIVE INGREDIENTS: NYSTATIN 100000 [USP'U]/1 mL
INACTIVE INGREDIENTS: ALCOHOL; CARBOXYMETHYLCELLULOSE SODIUM; SODIUM PHOSPHATE, DIBASIC; GLYCERIN; METHYLPARABEN; SODIUM PHOSPHATE, MONOBASIC; PROPYLPARABEN; WATER; SACCHARIN SODIUM; SUCROSE

NYSTATIN ORAL
SUSPENSION, USP

Rx Only

DESCRIPTION

Nystatin is an antimycotic polyene antibiotic obtained from Streptomyces noursei. Structural formula:

Nystatin Oral Suspension, USP, for oral administration contains 100,000 Nystatin units per mL. In addition, the yellow opaque suspension contains the following inactive ingredients : Alcohol (0.5% v/v), USP, Alcohol free Bubble Gum Flavoring, Carboxymethylcellulose Sodium, USP, Dibasic Sodium Phosphate, USP, Glycerin Natural 99.5%, USP, Methylparaben, NF, (Preservative), Monobasic Sodium Phosphate, USP, Propylparaben, NF, (Preservative), Purified Water, USP, Saccharin Sodium, USP, and Sucrose, NF.

CLINICAL PHARMACOLOGY

Pharmacokinetics

Gastrointestinal absorption of nystatin is insignificant. Most orally administered nystatin is passed unchanged in the stool. In patients with renal insufficiency receiving oral therapy with conventional dosage forms, significant plasma concentrations of nystatin may occasionally occur.

Microbiology

Nystatin is both fungistatic and fungicidal in vitro against a wide variety of yeasts and yeast-like fungi. Candida albicans demonstrates no significant resistance to nystatin in vitro on repeated subculture in increasing levels of nystatin; other Candida species become quite resistant. Generally, resistance does not develop in vivo. Nystatin acts by binding to sterols in the cell membrane of susceptible Candida species with a resultant change in membrane permeability allowing leakage of intracellular components. Nystatin exhibits no appreciable activity against bacteria, protozoa, or viruses.

INDICATIONS AND USAGE

Nystatin Oral Suspension, USP, is indicated for the treatment of candidiasis in the oral cavity.

CONTRAINDICATIONS

The preparation is contraindicated in patients with a history of hypersensitivity to any of its components.

PRECAUTIONS

General

This medication is not to be used for the treatment of systemic mycoses. Discontinue treatment if sensitization or irritation is reported during use.

Carcinogenesis, Mutagenesis, Impairment of Fertility

No long-term animal studies have been performed to evaluate carcinogenic potential. There also have been no studies to determine mutagenicity or whether this medication affects fertility in males or females.

Pregnancy

Teratogenic Effects

Category C

Animal reproduction studies have not been conducted with nystatin oral suspension. It is also not known whether nystatin oral suspension can cause fetal harm when administered to a pregnant woman or can affect reproduction capacity. Nystatin oral suspension should be given to a pregnant woman only if clearly needed.

Nursing Mothers

It is not known whether nystatin is excreted in human milk. Because many drugs are excreted in human milk, caution should be exercised when nystatin is administered to a nursing woman.

Pediatric Use

See DOSAGE AND ADMINISTRATION.

ADVERSE REACTIONS

Nystatin is well tolerated even with prolonged therapy. Oral irritation and sensitization have been reported. (See PRECAUTIONS: General).

Gastrointestinal: Diarrhea (including one case of bloody diarrhea), nausea, vomiting, gastrointestinal upset/disturbances.

Dermatologic: Rash, including urticaria has been reported rarely. Stevens-Johnson syndrome has been reported very rarely.

Other: Tachycardia, bronchospasm, facial swelling, and nonspecific myalgia have also been rarely reported.

To report SUSPECTED ADVERSE EVENTS, contact FDA at 1-800-FDA-1088 or www.fda.gov.

OVERDOSAGE

Oral doses of nystatin in excess of five million units daily have caused nausea and gastrointestinal upset. There have been no reports of serious toxic effects or superinfections (see CLINICAL PHARMACOLOGY: Pharmacokinetics).

DOSAGE AND ADMINISTRATION

Infants

2 mL (200,000 units) four times daily (in infants and young children, use dropper to place one-half of dose in each side of mouth and avoid feeding for 5 to 10 minutes).

NOTE: Limited clinical studies in premature and low birth weight infants indicate that 1 mL four times daily is effective.

Children and Adults

4 to 6 mL (400,000 to 600,000 units) four times daily (one-half of dose in each side of mouth). The preparation should be retained in the mouth as long as possible before swallowing.

Continue treatment for at least 48 hours after perioral symptoms have disappeared and cultures demonstrate eradication of Candida albicans.

HOW SUPPLIED

Nystatin Oral Suspension, USP, 100,000 Nystatin units per mL, is available as a bubble gum flavored, yellow opaque, ready-to-use suspension.

Nystatin Oral Suspension, USP, is available as follows:

NDC 17856-1008-01 NYSTATIN 100,000 UNITS/ML - 5 ML CUP 72 ct UD

Storage

Store at 20°C to 25°C (68° to 77°F) [See USP Controlled Room Temperature]

AVOID FREEZING

Rx Only

DISTRIBUTED BY:

ATLANTIC BIOLOGICALS CORP.

20101 N.E 16TH PLACE

MIAMI, FL 33179

PRINCIPAL DISPLAY PANEL - 480 mL Bottle

NDC 17856-1008-01

NYSTATIN 100,000 UNITS/ML - 5 ML CUP 72 ct UD

Rx only